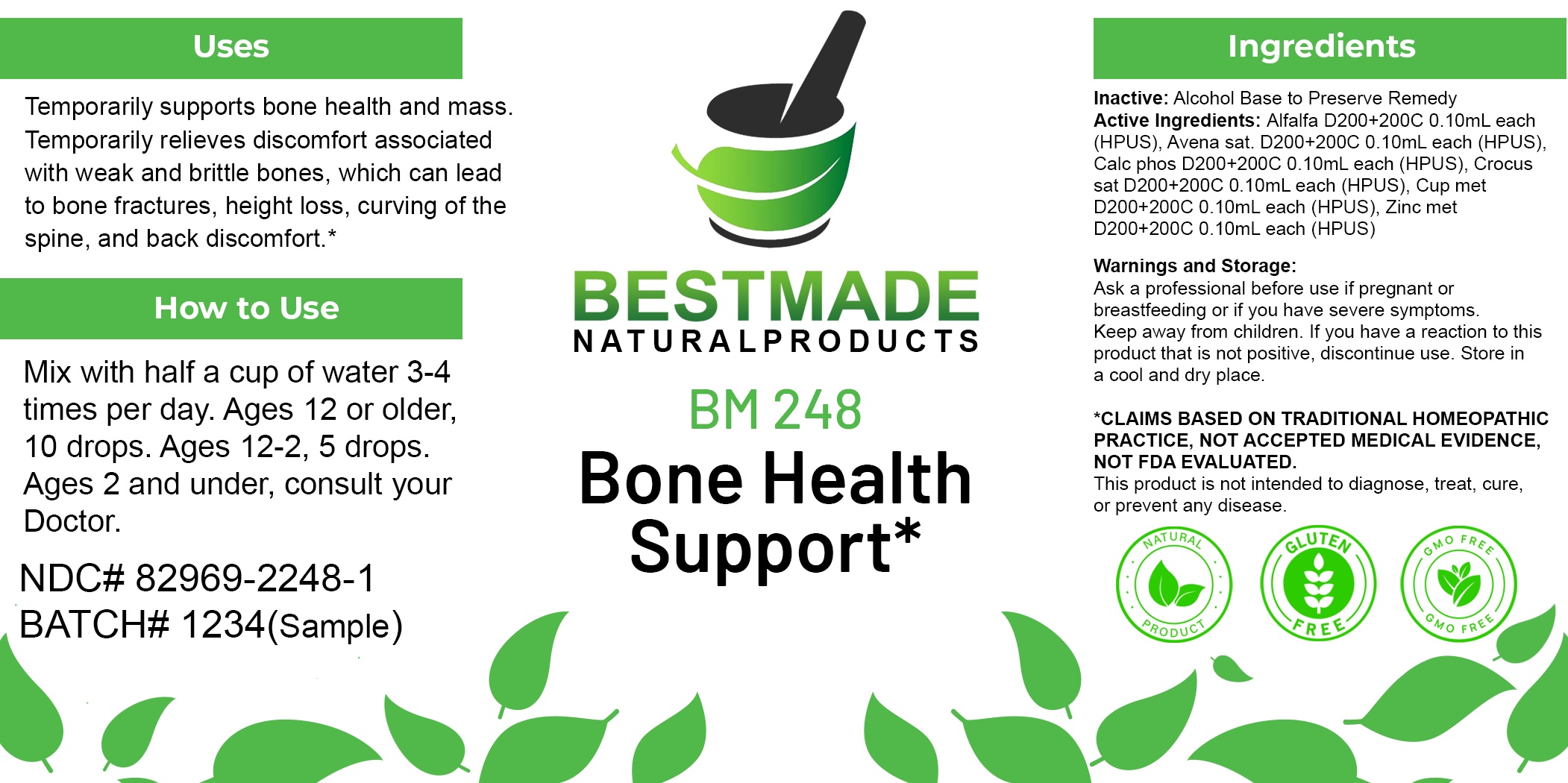 DRUG LABEL: Bestmade Natural Products BM248
NDC: 82969-2248 | Form: LIQUID
Manufacturer: Bestmade Natural Products
Category: homeopathic | Type: HUMAN OTC DRUG LABEL
Date: 20250305

ACTIVE INGREDIENTS: MEDICAGO SATIVA WHOLE 30 [hp_C]/30 [hp_C]; AVENA SATIVA FLOWERING TOP 30 [hp_C]/30 [hp_C]; ZINC 30 [hp_C]/30 [hp_C]; COPPER 30 [hp_C]/30 [hp_C]; TRIBASIC CALCIUM PHOSPHATE 30 [hp_C]/30 [hp_C]; SAFFRON 30 [hp_C]/30 [hp_C]
INACTIVE INGREDIENTS: ALCOHOL 30 [hp_C]/30 [hp_C]

BM248

DOSAGE AND ADMINISTRATION

How to Use

Mix with half a cup of water 3-4 times per day. Ages 12 or older, 10 drops. Ages 12-2, 5 drops. Ages 2 and under, consult your Doctor.

Inactive:

Alcohol Base to Preserve Product

ACTIVE INGREDIENTS

Alfalfa D200+200C 0.10mL each (HPUS), Avena sat. D200+200C 0.10mL each (HPUS), Calc phos D200+200C 0.10mL each (HPUS), Crocus sat D200+200C 0.10mL each (HPUS), Cup met D200+200C 0.10mL each (HPUS), Zinc met D200+200C 0.10mL each (HPUS)

KEEP OUT OF REACH OF CHILDREN

Warnings and Storage:

Ask a professional before use if pregnant or breastfeeding or if you have severe symptoms.

Keep away from children. If you have a reaction to this product that is not positive, discontinue use. Store in a cool and dry place

*CLAIMS BASED ON TRADITIONAL HOMEOPATHIC PRACTICE, NOT ACCEPTED MEDICAL EVIDENCE NOT FDA EVALUATED.
This product is not intended to diagnose, treat, cure, or prevent any disease.

Warnings and Storage:

Ask a professional before use if pregnant or breastfeeding or if you have severe symptoms.

Keep away from children. If you have a reaction to this product that is not positive, discontinue use. Store in a cool and dry place

*CLAIMS BASED ON TRADITIONAL HOMEOPATHIC PRACTICE, NOT ACCEPTED MEDICAL EVIDENCE NOT FDA EVALUATED.
This product is not intended to diagnose, treat, cure, or prevent any disease.

Uses
Temporarily supports bone health and mass. Temporarily relieves discomfort associated with weak and brittle bones, which can lead
to bone fractures, height loss, curving of the spine, and back discomfort.*

Uses
Temporarily supports bone health and mass. Temporarily relieves discomfort associated with weak and brittle bones, which can lead
to bone fractures, height loss, curving of the spine, and back discomfort.*

Entire package label